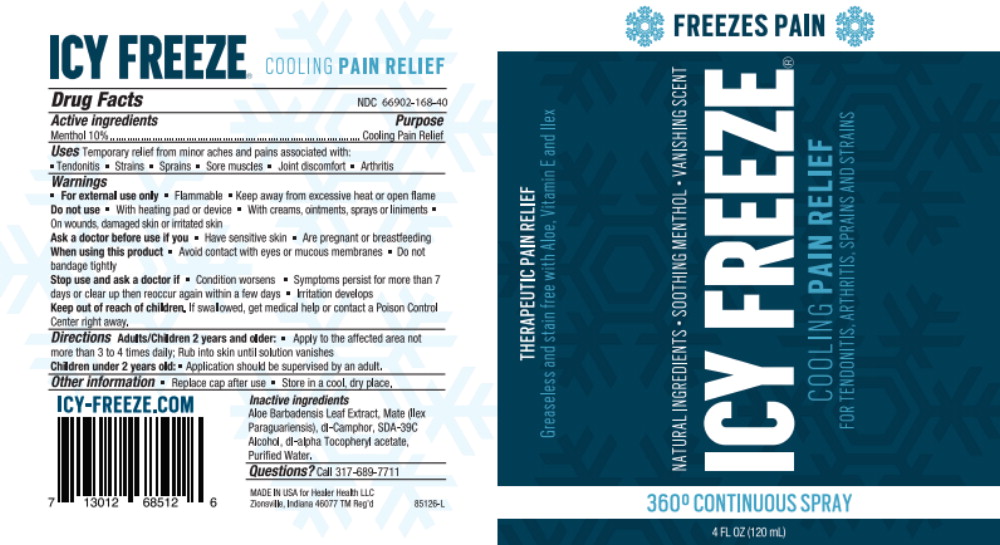 DRUG LABEL: ICY FREEZE
NDC: 66902-168 | Form: SPRAY
Manufacturer: Natural Essentials, Inc.
Category: otc | Type: HUMAN OTC DRUG LABEL
Date: 20250801

ACTIVE INGREDIENTS: MENTHOL, UNSPECIFIED FORM 100 mg/1 mL
INACTIVE INGREDIENTS: ALOE VERA LEAF; ILEX PARAGUARIENSIS LEAF; CAMPHOR (SYNTHETIC); ALCOHOL; .ALPHA.-TOCOPHEROL ACETATE; WATER

Drug Facts

NDC 66902-168-40

Active ingredients

Menthol 10%

Purpose

Cooling Pain Relief

Uses

Temporary relief from minor aches and pains associated with:

- Tendonitis
- Strains
- Sprains
- Sore muscles
- Joint discomfort
- Arthritis

Warnings

- For external use only
- Flammable
- Keep away from excessive heat or open flame

Do not use

- With heating pad or device
- With creams, ointments, sprays or liniments
- On wounds damaged skin or irritated skin

Ask a doctor before use if you

- Have sensitive skin
- Are pregnant or breastfeeding

When using this product

- Avoid contact with eyes or mucous membranes
- Do not bandage tightly

Stop use and ask a doctor if

- Condition worsens
- Symptoms persist for more than 7 days or clear up then reoccur again within a few days
- Irritation develops

Keep out of reach of children.If swallowed, get medical help or contact a Poison Control Center right away.

Directions

Adults/Children 2 years and older

- Apply to the affected area not more than 3 to 4 times daily; Rub into skin until solution vanishes

Children under 2 years old:

- Application should be supervised by an adult.

Other information

- Replace cap after use
- Store in a cool, dry place.

Inactive ingredients

Aloe Barbadensis Leaf Extract, Mate (Ilex Paraguariensis), dl-Camphor, SDA-39C Alcohol, dl-alpha Tocopheryl acetate, Purified Water.

Questions?

Call 317-689-7711

Principal Display Panel – 4 oz Can Label

THERAPEUTIC PAIN RELIEF

Greaseless and stain free with Aloe, Vitamin E and Ilex

NATURAL INGREDIENTS • SOOTHING MENTHOL • VANISHING SCENT

ICY FREEZE

COOLING PAIN RELIEF

FOR TENDONITIS, ARTHRITIS. SPRAINS AND STRAINS

FREEZES PAIN

360° CONTINUOUS SPRAY

4 FL OZ (120 mL)